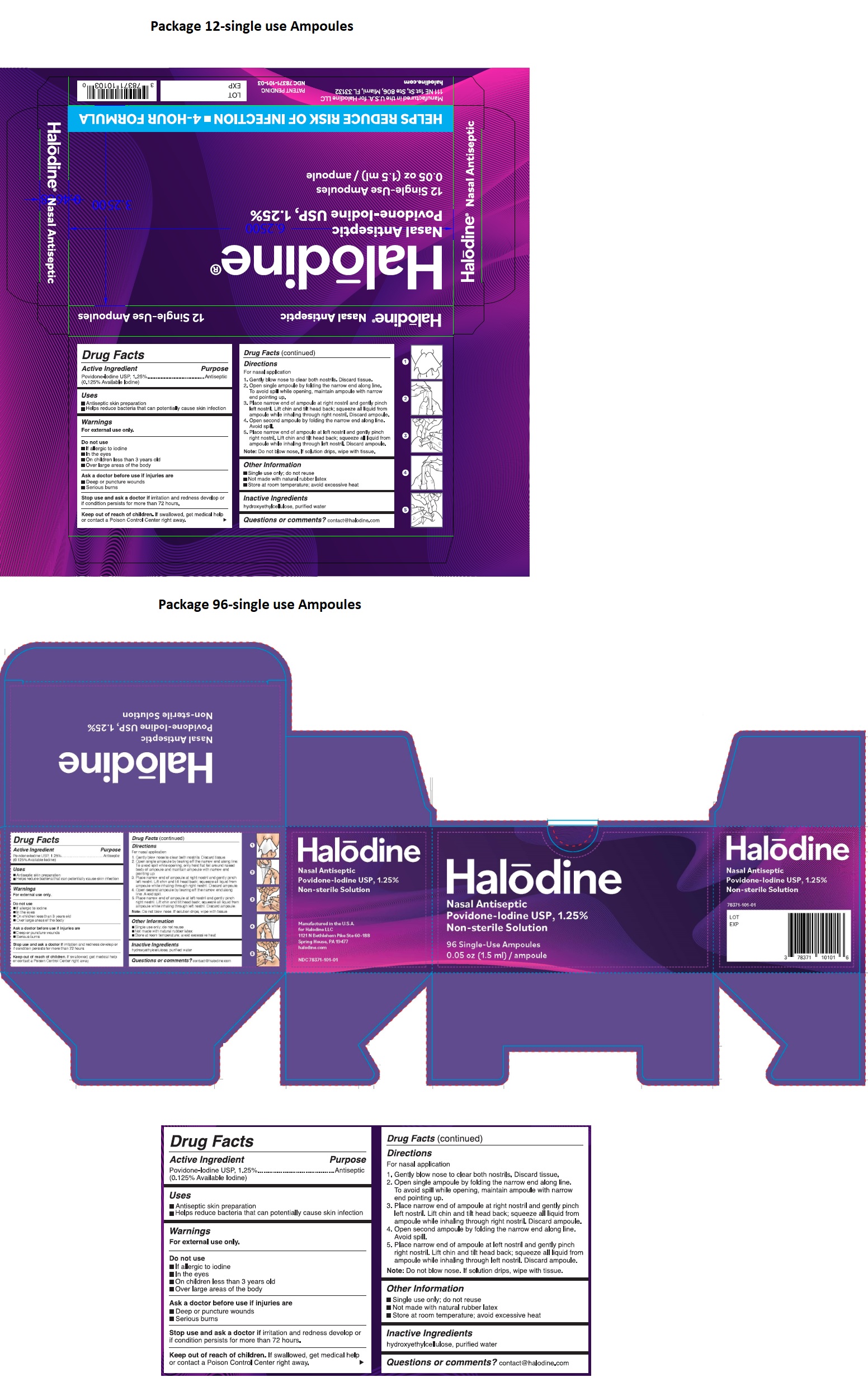 DRUG LABEL: Halodine Nasal Antiseptic
NDC: 78371-101 | Form: SOLUTION
Manufacturer: Halodine LLC
Category: otc | Type: HUMAN OTC DRUG LABEL
Date: 20210614

ACTIVE INGREDIENTS: POVIDONE-IODINE 1.25 mg/1 mL
INACTIVE INGREDIENTS: HYDROXYETHYL CELLULOSE, UNSPECIFIED; WATER

Halodine Nasal Antiseptic

Active Ingredient

Povidone-Iodine USP, 1.25%
(0.125% Available Iodine)

Purpose

Antiseptic

Uses

- Antiseptic skin preparation
- Helps reduce bacteria that can potentially cause skin infection

Warnings

For external use only.

Do not use

- If allergic to iodine
- In the eyes
- On children less than 3 years old
- Over large areas of the body

Ask a doctor before use if injuries are

- Deep or puncture wounds
- Serious burns

Stop use and ask a doctor if irritation and redness develop or if condition persists for more than 72 hours.

Keep out of reach of children. If swallowed, get medical help or contact a Poison Control Center right away.

Directions

For nasal application

1. Gently blow nose to clear both nostrils. Discard tissue.
2. Open single ampoule by folding the narrow end along line. To avoid spill while opening, maintain ampoule with narrow end pointing up.
3. Place narrow end of ampoule at right nostril and gently pinch left nostril. Lift chin and tilt head back; squeeze all liquid from ampoule while inhaling through right nostril. Discard ampoule.
4. Open second ampoule by folding the narrow end along line. Avoid spill.
5. Place narrow end of ampoule at left nostril and gently pinch right nostril. Lift chin and tilt head back; squeeze all liquid from ampoule while inhaling through left nostril. Discard ampoule.

Note: Do not blow nose. If solution drips, wipe with tissue.

Other Information

- Single use only; do not reuse
- Not made with natural rubber latex
- Store at room temperature; avoid excessive heat

Inactive Ingredients

hydroxyethylcellulose, purified water

Questions or comments?

contact@halodine.com

HELPS REDUCE RISK OF INFECTION • 4-HOUR FORMULA

Non-sterile Solution

Manufactured in the U.S.A. for Halodine LLC

111 NE 1st St, Ste 806, Miami, FL 33132

halodine.com